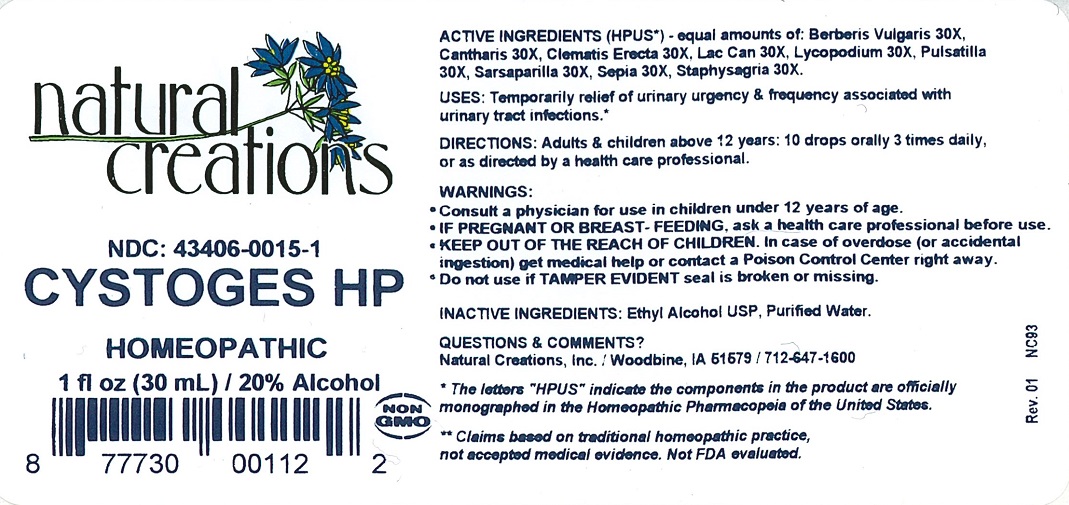 DRUG LABEL: CYSTOGES HP
NDC: 43406-0015 | Form: LIQUID
Manufacturer: Natural Creations, Inc.
Category: homeopathic | Type: HUMAN OTC DRUG LABEL
Date: 20251121

ACTIVE INGREDIENTS: BERBERIS VULGARIS ROOT BARK 30 [hp_X]/1 mL; LYTTA VESICATORIA 30 [hp_X]/1 mL; CLEMATIS RECTA FLOWERING TOP 30 [hp_X]/1 mL; CANIS LUPUS FAMILIARIS MILK 30 [hp_X]/1 mL; LYCOPODIUM CLAVATUM SPORE 30 [hp_X]/1 mL; PULSATILLA VULGARIS 30 [hp_X]/1 mL; SARSAPARILLA 30 [hp_X]/1 mL; SEPIA OFFICINALIS JUICE 30 [hp_X]/1 mL; DELPHINIUM STAPHISAGRIA SEED 30 [hp_X]/1 mL
INACTIVE INGREDIENTS: WATER; ALCOHOL

CYSTOGES HP

ACTIVE INGREDIENT

Active Ingredients (HPUS*) - equal amounts of: Berberis Vulgaris 30X, Cantharis 30X, Clematis Erecta 30X, Lac Caninum 30X, Lycopodium Clavatum 30X, Pulsatilla 30X, Sarsaparilla 30X, Sepia 30X, Staphysagria 30X

INDICATIONS AND USAGE

USES: Temporarily relief of urinary urgency & frequency associated with urinary tract infections.**

WARNING:

- Consult a physician for use in children under 12 years of age.
- IF PREGNANT OR BREAST-FEEDING, ask a health care professional before use.
- KEEP OUT OF THE REACH OF CHILDREN. In case of overdose (or accidental ingestion) get medical help or contact a Poison Control Center right away.
- Do not use if TAMPER EVIDENT seal is broken or missing.

DOSAGE AND ADMINISTRATION

DIRECTIONS: Adults and children above 12 years: 10 drops orally 3 times daily, or as directed by a health care professional.

REFERENCES

*The letters "HPUS" indicate the components in the product are officially monographed in the Homeopathic Pharmacopeia of the United States.

**Claims based on traditional homeopathic practice, not accepted medical evidence. Not FDA evaluated.

INACTIVE INGREDIENTS: Ethyl Alcohol USP, Purified Water.

QUESTIONS AND COMMENTS?

Natural Creations / Woodbine, IA 51579 / 712-647-1600

PURPOSE

USES: Temporarily relief of urinary urgency & frequency associated with urinary tract infections.**

KEEP OUT OF REACH OF CHILDREN

KEEP OUT OF THE REACH OF CHILDREN. In case of overdose (or accidental ingestion) get medical help or contact a Poison Control Center.

PACKAGE LABEL

NDC: 43406-0015-1

CYSTOGES HP

HOMEOPATHIC

1 fl oz (30 mL) / 20% Alcohol